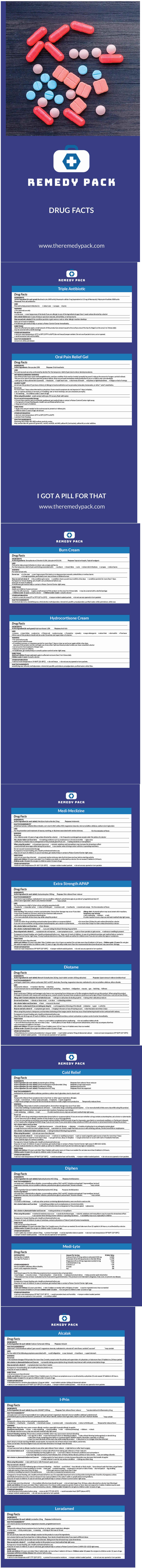 DRUG LABEL: Diphen
NDC: 82652-021 | Form: KIT | Route: TOPICAL
Manufacturer: Remedy Pack LLC
Category: otc | Type: HUMAN OTC DRUG LABEL
Date: 20220711

ACTIVE INGREDIENTS: benzocaine 200 mg/1 g; Benzalkonium Chloride 1.3 mg/1 g; Lidocaine Hydrochloride 5 mg/1 g; HYDROCORTISONE ACETATE 10 mg/1 g; Bacitracin Zinc 400 [USP'U]/1 g; Neomycin Sulfate 3.5 mg/1 g; Polymyxin B Sulfate 5000 [USP'U]/1 g; Calcium Carbonate 420 mg/1 1; Ibuprofen 200 mg/1 1; Loratadine 10 mg/1 1; Acetaminophen 325 mg/1 1; Dextromethorphan Hydrobromide 15 mg/1 1; Guaifenesin 200 mg/1 1; Phenylephrine Hydrochloride 5 mg/1 1; Diphenhydramine Hydrochloride 25 mg/1 1; Calcium Carbonate 27 mg/1 1; Potassium Chloride 80 mg/1 1; Magnesium Oxide 20 mg/1 1; Meclizine Hydrochloride 25 mg/1 1; Acetaminophen 500 mg/1 1; Bismuth Subsalicylate 262 mg/1 1
INACTIVE INGREDIENTS: polyethylene glycol 400; polyethylene glycol 3350; peppermint oil; saccharin sodium; sorbic acid; Alcohol; Methylparaben; Mineral Oil; Paraffin; Propylparaben; Water; White Petrolatum; White Wax; Alcohol; Methylparaben; Mineral Oil; Paraffin; Petrolatum; Propylparaben; Water; White Wax; Polyethylene Glycol 3350; Polyethylene Glycol 400; Saccharin Sodium; FD&C Blue No. 1; FD&C Green No. 3; D&C Green No. 5; FD&C Red No. 3; D&C Red No. 28; FD&C Red No. 40; FD&C Yellow No. 5; FD&C Yellow No. 6; Aspartame; Croscarmellose Sodium; Acacia; Magnesium Stearate; Maltodextrin; Mineral Oil; Sorbitol; Sucrose; Carnauba Wax; Starch, Corn; Hypromellose, Unspecified; Ferric Oxide Red; Lactose, Unspecified Form; Magnesium Stearate; Microcrystalline Cellulose; Polydextrose; Polyethylene Glycol, Unspecified; Polyvinyl Alcohol, Unspecified; Povidone K30; Silicon Dioxide; SODIUM STARCH GLYCOLATE TYPE A; Stearic Acid; Talc; Titanium Dioxide; Starch, Corn; Lactose Monohydrate; Magnesium Stearate; Maltodextrin; Microcrystalline Cellulose; Povidone, Unspecified; SODIUM STARCH GLYCOLATE TYPE A; Stearic Acid; Carnauba Wax; Silicon Dioxide; Croscarmellose Sodium; D&C Red No. 27; Anhydrous Dibasic Calcium Phosphate; Hypromellose, Unspecified; Lactose, Unspecified Form; Magnesium Stearate; Microcrystalline Cellulose; Polyethylene Glycol, Unspecified; Titanium Dioxide; Microcrystalline Cellulose; Silicon Dioxide; Stearic Acid; Magnesium Stearate; Anhydrous Lactose; Silicon Dioxide; Starch, Corn; D&C Yellow No. 10; Magnesium Stearate; Microcrystalline Cellulose; SODIUM STARCH GLYCOLATE TYPE A; Starch, Corn; Hypromellose, Unspecified; Maltodextrin; Microcrystalline Cellulose; Polyethylene Glycol, Unspecified; SODIUM STARCH GLYCOLATE TYPE A; Stearic Acid; Titanium Dioxide; Acacia; Aspartame; Calcium Carbonate; D&C Red No. 27; Dextrates; Magnesium Stearate; Maltodextrin; Microcrystalline Cellulose; Silicon Dioxide

Diphen

REMEDY PACK

Burn Cream

Drug Facts

INGREDIENTS

Active ingredients

Benzalkonium Chloride 0.13%, Lidocaine HCl 0.5%

Purpose

Topical antiseptic, Topicall analgesic

USES

First aid to help prevent infection in minor cuts, scrapes and burns.

For the temporary relief of pain and itching associated with:

- sunburn
- insect bites
- cuts
- minor skin irritations
- scrapes
- minor burns

WARNING

For external use only.

Do not use

- in the eyes
- over large areas of the body or on deep puncture wounds, animal bites, or serious burns
- in large quantities, particularly over raw surfaces or blistered areas

Stop use and ask doctor if

- the condition gets worse
- condition clears up and recurs within a few days
- condition persists for more than 7 days

PREGNANCY OR BREAST FEEDING

If pregnant or breast feeding, ask a health care professional before use.

Keep out of reach of children.

If swallowed, get medical help or contact a Poison Control Center right away.

DIRECTIONS

Adults and children 2 years and over:

- clean the affected area
- apply a small amount of this product on the area 3 to 4 times daily
- may be covered with a sterile bandage
- Children under 12 years: consult a doctor
- Children under 2 years: consult a doctor

OTHER INFORMATION

- store in a cool, dry area 59° to 79°F (15° to 25°C)
- tamper evident sealed packets
- do not use any opened or torn packets

INACTIVE INGREDIENTS

decolorized aloe vera, emulsifying wax, ethyl alcohol, methylparaben, mineral oil, paraffin, propylparaben, purified water, white petrolatum, white wax

Triple Antibiotic

Drug Facts

INGREDIENTS

Active Ingredient (in each gram)

Bacitracin zinc (400 units), Neomycin sulfate 5 mg (equivalent to 3.5 mg of Neomycin), Polymyxin-B sulfate 5000 units

Purposes

First aid antibiotics

USES

First aid to help prevent infection in:

- minor cuts
- scrapes
- burns

WARNING

- For external use only

Do not use

- in the eyes
- over large areas of the body if you are allergic to any of the ingredients longer than 1 week unless directed by a doctor

Ask a doctor before use

in case of deep or puncture wounds, animal bites, or serious burns

Stop use and ask a doctor if

the condition persists or gets worse a rash or other allergic reaction develops

Keep out of reach of children.

If swallowed, get medical help or contact a Poison Control Center immediately.

DIRECTIONS

clean the affected area apply a small amount of this product (an amount equal to the surface area of the tip of a finger) on the area 1 to 3 times daily
may be covered with a sterile bandage

OTHER INFORMATION

- store at room temperature 15°C to 30°C (59°F to 86°F) (do not freeze) tamper evident. Do not use if packet is torn, cut or opened.
- avoid excessive heat and humidity

INACTIVE INGREDIENTS

mineral oil, white petrolatum

Hydrocortisone Cream

Drug Facts

INGREDIENTS

Active Ingredient (in each gram)

Hydrocortisone 1.0%

Purpose

Anti-Itch

USES

- eczema
- insect bites
- poison ivy
- Poison oak
- poison sumac
- Cosmetics
- jewelry
- soaps detergents
- seborrheic
- dermatitis
- Psoriasas

Other uses of this product should only be under the advice and supervision of a doctor.

WARNING

- For external use only
- avoid contact with the eyes
- if condition worsens, or symptoms persist for more than 7 days or clear up and occur again within a few days, stop use of this product and do not begin use of any other hydrocortisone product unless you have consulted a doctor

- do not use for the treatment of diaper rash.

- Keep out of reach of children.
- If swallowed, get medical help or consult a poison control center right away.

DIRECTIONS

Adult and children (2 years and over): apply to affected not more than 3 to 4 times daily

Children under 2 years: Consult a doctor.

OTHER INFORMATION

- store at room temperature 59-86ºF (15-30ºC)
- do not freeze
- do not use any opened or torn packets.

INACTIVE INGREDIENTS

emulsifying wax, ethanol, methylparaben, mineral oil, paraffin, petrolatum, propylparaben, purified water, white Wax.

Oral Pain Relief Gel

Drug Facts

INGREDIENTS

Active ingredients

Benzocaine 20%

Purpose

Oral Anesthetic

USES

For oral mucosal use only, as directed by dentist. For the temporary relief of pain due to minor dental procedures.

WARNINGS

METHEMOGLOBINEMIA WARNING

Use of this product may cause methemoglobinemia, a serious condition that must be treated promptly because it reduces the amount of oxygen carried in blood.

This can occur even if you have used this product before. Stop use and seek immediate medical attention if you or a child in your care develops:

- pale, gray, or blue colored skin (cyanosis)
- headache
- rapid heart rate
- shortness of breath
- dizziness or lightheadedness
- fatigue or lack of energy

ALLERGY ALERT

do not use this product if you have a history of allergy to local anesthetics such as procaine, butacaine, benzocaine, or other " caine" anesthetics.

Do not use

For more than 7 days unless directed by a physician. If sore mouth symptoms do not improve in 7 days; irritation, pain, or redness persists or worsens; or if swelling, rash or fever develops, see your physician promptly.

- for teething
- in children under 2 years of age

When using this product

avoid contact with eyes. If it occurs, flush with water.

Do not exceed recommended dosage.

- If more than used for pain is accidently swallowed, get medical help or contact a Poison Control Center right away.

PREGNANCY OR BREAST FEEDING

- If pregnant or breast feeding,ask a health care professional before use.

- Keep out of reach of children.

DIRECTIONS

- Apply only amount needed to the oral mucosa to prevent or relieve pain.
- children under 2 years of age: do not use

OTHER INFORMATION

- store at room temperature 15°C to 30°C (59°F to 86°F)
- protect from freezing

INACTIVE INGREDIENTS

Flavoring, PEG 3350, PEG 400, sodium sacchrin, water.

May contain blue #1, green #3, green #5 , red #3, red #28, red #40, yellow #5, (tartrazine), yellow #6, as color additive.

Alcalak

Drug Facts

INGREDIENTS

Active ingredient (in each tablet)

Calcium Carbonate 420mg

Purpose

Antacid

INACTIVE INGREDIENTS [may contain]

aspartame, croscarmellose sodium, gum acacia, magnesium stearate, maltodextrin, mineral oil, mint flavor, sorbitol, sucrose

USES

For the relief of the following symptoms associated with

- acid indigestion
- sour stomach
- heartburn
- upset stomach

WARNING

Do not use

- the maximum dosage of this product for more than 2 weeks, except under the advice and supervision of a physician, or take more than 19 tablets in a 24 hour period.

Ask a doctor or pharmacist before use if you are

- presently taking a prescription drug. Antacids may interact with certain prescription drugs.

Stop use and ask a doctor if

- symptoms last more than 2 weeks

PREGNANCY OR BREAST FEEDING

If pregnant or breastfeeding, ask a health professional before use.

Keep out of reach of children.

DIRECTIONS

- do not use more than directed

Adults and children: (12 years and older) Chew 2 tablets every 2 or 3 hours as symptoms occur or as directed by a physician. Do not exceed 19 tablets in 24 hours.

Children under 12 years: Do not give to children under 12 years of age.

OTHER INFORMATION

- Phenylketonurics: contains phenylalanine 1.5mg per tablet
- each tablet contains 168mg of elemental calcium
- store at room temperature 59º-86ºF (15º-30ºC) in a dry place
- tamper-evident sealed packets
- do not use any opened or torn packets

Cold Relief

Drug Facts

INGREDIENTS

ACTIVE INGREDIENT

Active ingredient (in each tablet): Acetaminophen 325mg | Purpose: Pain reliever/ fever reducer
Active ingredient (in each tablet): Dextromethorphan Hydrobromide 15mg | Purpose: Cough suppressant
Active ingredient (in each tablet): Guaifenesin 200mg | Purpose: Expectorant
Active ingredient (in each tablet): Phenylephrine HCl 5mg | Purpose: Nasal decongestant

INACTIVE INGREDIENTS*

maltodextrin, microcrystalline cellulose, povidone, sodium starch glycolate, starch, stearic acid

USES

Temporarily relieves these symptoms due to hay fever or other upper respiratory allergies

- cough
- sore throat
- minor aches and pains
- headache
- nasal congestion
- helps loosen phlegm (mucus) and thin bronchial secretions to make coughs more productive

Temporarily reduces fever.

WARNING

Liver warning

This product contains acetaminophen. Severe liver damage may occur if you take:

- more than 4,000mg of acetaminophen in 24 hours
- with other drugs containing acetaminophen
- 3 or more alcoholic drinks every day while using this product

Allergy alert

Acetaminophen may cause severe skin reactions. Symptoms may include:

- skin reddening
- blisters
- rash

If a skin reaction occurs, stop use and seek medical help right away.

Do not use

- with any other drug containing acetaminophen (prescription or nonprescription). If you are not sure whether a drug contains acetaminophen, ask a doctor or pharmacist.
- if you have ever had an allergic reaction to this product or any of the ingredients.
- if you are now taking a prescription monoamine oxidase inhibitor (MAOI) (certain drugs for depression, psychiatric or emotional conditions, or Parkinson's disease), or for 2 weeks after stopping the MAOI drug. If you do not know if your prescription drug contains an MAOI, ask a doctor or pharmacist before taking this product.

Ask a doctor before use if you have

- liver disease
- heart disease
- high blood pressure
- thyroid disease
- diabetes
- trouble urinating due to an enlarged prostate gland
- cough that occurs with too much phlegm (mucus)
- persistent or chronic cough that lasts as occurs with smoking, asthma, chronic bronchitis or emphysema

Ask a doctor or pharmacist before use if you are

- taking the blood thinning drug warfarin

When using this product

- do not use more than directed

Stop use and ask a doctor if

- new symptoms occur
- redness or swelling is present
- pain or nasal congestion gets worse or lasts for more than 7 days
- fever gets worse or lasts for more than 3 days
- you get nervous, dizzy or sleepless
- cough comes back or occurs with rash or headache that lasts.

These could be signs of a serious condition.

PREGNANCY OR BREAST FEEDING

If pregnant or breast-feeding, ask a health professional before use.

Keep out of reach of children. In case of overdose, get medical help or contact a Poison Control Center right away (1-800-222-1222).

Prompt medical attention is critical for adults as well as for children even if you do not notice any signs or symptoms.

DIRECTIONS

Adults and children: (12 years and older) Take 2 tablets with water every 6- 8 hours as needed. Do not take more than 8 tablets in 24 hours.

Children under 12 years: Do not give to children under 12 years of age.

OTHER INFORMATION

- store at room temperature 59º-86ºF (15º-30ºC)
- avoid excessive heat and humidity
- tamper-evident sealed packets
- do not use any opened or torn packets

Medi-Meclizine

Drug Facts

INGREDIENTS

Active ingredient (in each tablet)

Meclizine Hydrochloride 25mg

Purpose

Antiemetic

INACTIVE INGREDIENTS*

anhydrous lactose, colloidal silicon dioxide, corn starch, D&C yellow #10, magnesium stearate, microcrystalline cellulose, sodium starch glycolate

USES

For the prevention and treatment of nausea, vomiting, or dizziness associated with motion sickness.

For the reduction of fever.

WARNING

Do not use

- for children under 12 years of age unless directed by a doctor
- for frequent or prolonged use except under the advice of a doctor

Ask a doctor before use if you have

- breathing problems such as emphysema or chronic bronchitis
- glaucoma
- difficulty in urination due to enlargement of the prostate gland if you are
- taking sedatives or tranquilizers

When using this product

- drowsiness may occur
- alcohol, sedatives and tranquilizers may increase the drowsiness effect
- avoid alcoholic beverages while taking this product
- use caution when driving a motor vehicle or operating machinery

Do not exceed recommended dosage.

PREGNANCY OR BREAST FEEDING

If pregnant or breast-feeding, ask a health professional before use.

Keep out of reach of children. In case of overdose, get medical help or contact a Poison Control Center right away.

DIRECTIONS

- do not use more than directed
- to prevent motion sickness, take the first dose one hour before starting activity

Adults and children: (12 years and older) 1 to 2 tablets once daily or as directed by a doctor. Do not exceed 2 tablets in 24 hours.

Children under 12 years: Do not give to children under 12 years of age.

OTHER INFORMATION

- store at room temperature 59- 86º F (15-30ºC)
- tamper-evident sealed packets
- do not use any opened or torn packets

I-Prin

Drug Facts

INGREDIENTS

Active ingredient (in each tablet)

Ibuprofen (NSAID [nonsteroidal anti-inflammatory drug]) 200mg

Purpose

Pain reliever/fever reducer

INACTIVE INGREDIENTS [may contain]

carnauba wax, corn starch, hypromellose, iron oxide red, lactose, magnesium stearate, microcrystalline cellulose, polydextrose, polyethylene glycol, polyvinyl alcohol, povidone (K-30), silicon dioxide, sodium starch glycolate, stearic acid, talc, titanium dioxide

USES

Temporarily relieves minor aches and pains associated with

- headache
- toothache
- backache
- menstrual cramps
- common cold
- muscular aches
- minor arthritis pain

Temporarily reduces fever.

WARNING

Allergy alert

Ibuprofen may cause a severe allergic reaction, especially in people allergic to aspirin.

Symptoms may include:

- hives
- skin reddening
- facial swelling
- rash
- asthma (wheezing)
- blisters
- shock

If an allergic reaction occurs, stop use and seek medical help right away.

Stomach bleeding warning

This product contains an NSAID, which may cause severe stomach bleeding.

The chance is higher if you:

- are age 60 or older
- have had stomach ulcers or bleeding problems
- take a blood thinning (anticoagulant) or steroid drug
- take other drugs containing prescription or nonprescription NSAIDs (aspirin, ibuprofen, naproxen, or others)
- have 3 or more alcoholic drinks every day while using this product
- take more or for a longer time than directed

Heart attack or stroke warning: NSAIDS, except aspirin, increase the risk of heart attack, heart failure, and stroke.

These can be fatal. The risk is higher if you use more than directed or for longer than directed.

Do not use

- if you have ever had an allergic reaction to any other pain reliever/ fever reducer
- right before or after heart surgery

Ask a doctor before use if

- you have problems or serious side effects from taking pain relievers or fever reducers
- stomach bleeding warning applies to you
- you have a history of stomach problems such as heartburn
- you have high blood pressure, heart disease, liver cirrhosis, kidney disease, asthma or had a stroke
- you are taking a diuretic

Ask a doctor or pharmacist before use if you are

- taking aspirin for heart attack or stroke, because ibuprofen may decrease this benefit of aspirin
- under a doctor's care for any serious condition
- taking any other drug

When using this product

- take with food or milk if stomach upset occurs

Stop use and ask a doctor if

- you experience any of the following signs of stomach bleeding:
  - feel faint
  - vomit blood
  - have bloody or black stools
  - have stomach pain that does not get better
- you have symptoms of heart problems or stroke
  - chest pain
  - trouble breathing
  - weakness in one part or side of body
  - slurred speech
  - leg swelling
- pain gets worse or lasts more than 10 days
- fever gets worse or lasts more than 3 days
- redness or swelling is present in the painful area
- any new or unexpected symptoms occur

PREGNANCY OR BREAST FEEDING

If pregnant or breast-feeding, ask a health professional before use. It is especially important not to use ibuprofen during the last 3 months of pregnancy unless specifically directed to do so by a doctor because it may cause problems in the unborn child or complications during delivery.

Keep out of reach of children. In case of overdose, get medical help or contact a Poison Control Center right away.

DIRECTIONS

- do not take more than directed
- the smallest effective dose should be used
- do not take longer than 10 days, unless directed by a doctor (see Warnings)

Adults and children: (12 years and older) Take 1 tablet every 4 to 6 hours while symptoms persist. If pain or fever does not respond to 1 tablet, 2 tablets may be used. Do not exceed 6 tablets in 24 hours, unless directed by a doctor.

Children under 12 years: Do not give to children under 12 years of age.

OTHER INFORMATION

- read all product information before using
- store at 68-77°F (20-25°C)
- avoid excessive heat 104°F (above 40°C)
- tamper-evident sealed packets
- do not use any opened or torn packets

Diphen

Drug Facts

INGREDIENTS

Active ingredient (in each tablet)

Diphenhydramine HCl 25mg

Purpose

Antihistamine

INACTIVE INGREDIENTS [may contain]

carnauba wax, colloidal silicon dioxide, croscarmellose sodium, D&C red #27, dicalcium phosphate, hypromellose, lactose, magnesium stearate, microcrystalline cellulose, polyethylene glycol, polysorbate, titanium dioxide

USES

Active ingredients

Diphenhydramine HCl 25mg

Purpose

Antihistamine

Inactive Ingredients [may contain]

carnauba wax, colloidal silicon dioxide, croscarmellose sodium, D&C red #27, dicalcium phosphate, hypromellose, lactose, magnesium stearate, microcrystalline cellulose, polyethylene glycol, polysorbate, titanium dioxide

WARNING

Do not use

- to make a child sleepy
- with any other product containing diphenhydramine, even one that is used on skin

Ask a doctor before use if you have

- a breathing problem such as emphysema or chronic bronchitis
- difficulty in urination due to enlargement of the prostate gland
- glaucoma

Ask a doctor or pharmacist before use if you are

- taking sedatives or tranquilizers

When using this product

- marked drowsiness may occur
- avoid alcohol beverages
- alcohol, sedatives and tranquilizers may increase the drowsiness effect
- use caution when driving a motor vehicle or operating machinery
- excitability may occur, especially in children

PREGNANCY OR BREAST FEEDING

If pregnant or breast-feeding, ask a health professional before use.

Keep out of reach of children. In case of overdose, contact a physician or Poison Control Center immediately.

DIRECTIONS

- do not use more than directed

Adults and children: (12 years and older) Take 1 to 2 caplets every 4 to 6 hours as needed. Do not take more than 12 caplets in 24 hours, or as directed by a doctor.

Children under 12 years: Do not give to children under 12 years of age.

OTHER INFORMATION

- each caplet may contain: calcium 25mg
- protect from light
- use by expiration date on packet
- store at room temperature 59º-86ºF (15º-30ºC)
- tamper-evident sealed packets
- do not use any opened or torn packets

Extra Strength APAP

Drug Facts

INGREDIENTS

Active ingredient (in each tablet)

Acetaminophen 500mg

Purpose

Pain reliever/fever reducer

INACTIVE INGREDIENTS [may contain]

corn starch, hypromellose, maltodextrin, microcrystalline cellulose, polyethylene glycol, povidone, pregelatinized starch, sodium starch glycolate, stearic acid, titanium dioxide

USES

For the temporary relief of minor aches and pains associated with

- headache
- muscular aches
- minor arthritis pain
- common cold
- toothache
- menstrual cramps

For the reduction of fever.

WARNING

Liver warning

This product contains acetaminophen. Severe liver damage may occur if you take:

- more than 8 tablets in 24 hours, which is the maximum daily amount
- with other drugs containing acetaminophen
- 3 or more alcoholic drinks every day while using this product

Allergy alert

Acetaminophen may cause severe skin reactions.

Symptoms may include:

- skin reddening
- blisters
- rash

If a skin reaction occurs, stop use and seek medical help right away.

Do not use

- with any other drug containing acetaminophen (prescription or nonprescription). If you are not sure whether a drug contains acetaminophen, ask a doctor or pharmacist.
- for more than 10 days for pain unless directed by a doctor
- for more than 3 days for fever unless directed by a doctor

Ask a doctor before use if you have

- liver disease

Ask a doctor or pharmacist before use if

- you are taking the blood thinning drug warfarin

Stop using and ask a doctor if

- symptoms do not improve
- new symptoms occur
- pain or fever persists or gets worse
- redness or swelling is present

PREGNANCY OR BREAST FEEDING

If pregnant or breast-feeding, ask a health professional before use.

Keep out of reach of children. In case of accidental overdose, get medical help or contact a Poison Control Center right away. Prompt medical attention is critical for adults as well as for children even if you do not notice any signs or symptoms.

DIRECTIONS

- do not use more than directed

Adults and children: (12 years and older) Take 2 tablets every 4 to 6 hours as needed. Do not take more than 8 tablets in 24 hours.

Children under 12 years: Do not give this adult strength product to children under 12 years of age; this will provide more than the recommended dose (overdose) and may cause liver damage.

OTHER INFORMATION

- store at room temperature 59º-86ºF (15º-30ºC)
- tamper-evident sealed packets
- do not use any opened or torn packets

Loradamed

Drug Facts

INGREDIENTS

Active ingredient (in each tablet)

Loratadine 10mg

Purpose

Antihistamine

INACTIVE INGREDIENTS*

corn starch, lactose monohydrate, magnesium stearate, pregelatinized starch

USES

Temporarily relieves these symptoms due to hay fever or other upper respiratory allergies

- runny nose
- itchy, watery eyes
- sneezing
- itching of the nose or throat

WARNING

Do not use if you have ever had an allergic reaction to this product or any of its ingredients.

Ask a doctor before use if you have liver or kidney disease. Your doctor should determine if you need a different dose.

When using this product do not take more than directed. Taking more than directed may cause drowsiness.

Stop use and ask a doctor if

- an allergic reaction to this product occurs. Seek medical help right away.

PREGNANCY OR BREAST FEEDING

If pregnant or breast-feeding, ask a health professional before use.

Keep out of reach of children. In case of overdose, get medical help or contact a Poison Control Center (1-800-222-1222) right away.

DIRECTIONS

Adults and children: (12 years and older) Take 1 tablet daily; not more than 1 tablet in 24 hours.

Children under 12 years: Do not give to children under 12 years of age.

Consumers with liver or kidney disease: Ask a doctor before using.

OTHER INFORMATION

- store at room temperature 68º-77ºF (20º-25ºC)
- protect from excessive moisture
- tamper-evident sealed packets
- do not use any opened or torn packets

Medi-Lyte

Drug Facts

INFORMATION

Serving Size: 2 tablets

Servings Per Packet: 1

OTHER INGREDIENTS

microcrystalline cellulose, silicon dioxide, stearic acid, magnesium stearate

ACTIVE INGREDIENT

Amount Per Serving | % Daily Value
Calcium (from 27.0 mg calcium carbonate) 10.8 mg | 1.06%
Potassium (from 80 mg potassium chloride) 40mg | 1.15%
Magnesium (from 20 mg magnesium oxide) 12 mg | 3.0%
Carbohydrates 6 mg | >1%
Calories 1.5 | >1%
Protein | 0%
Fat | 0%

USES

Nutritional support for the following symptoms due to excessive loss of perspiration

- heat fatigue
- muscle cramps
- heat exhaustion
- heat stroke
- replaces lost electrolytes
- helps provide rapid rehydration

*This statement has not been evaluated by the Food and Drug administration. This product is not intended to diagnose, treat, cure, or prevent any disease.

WARNING

PREGNANCY OR BREAST FEEDING

If pregnant or breast-feeding, ask a health professional before use.

Keep out of reach of children. In case of overdose, get medical help or contact a Poison Control Center right away.

DIRECTIONS

Adults and children: (12 years and older)

- take 2 tablets as needed with a full glass of water
- may be repeated every hour as needed
- do not exceed 20 tablets in 24 hours

Children under 12 years:

- Do not give to children under 12 years of age

OTHER INFORMATION

- store at room temperature 59º-86º F (15º-30º C)
- avoid excessive heat and humidity
- tamper-evident sealed packets
- do not use any opened or torn packets
- no sodium added

Diotame

Drug Facts

INGREDIENTS

Active ingredient (in each tablet)

Bismuth Subsalicylate 262mg (each tablet contains 102mg salicylate)

Purpose

Upset stomach reliever/antidiarrheal

INACTIVE INGREDIENTS*

acacia gum, aspartame, calcium carbonate, D&C red #27, dextrates, flavoring, magnesium stearate, maltodextrin, microcrystalline cellulose, silicon dioxide

USES

Temporarily relieves

- travelers' diarrhea
- diarrhea
- upset stomach due to overindulgence in food and drink, including
  - heartburn
  - indigestion
  - nausea
  - gas
  - belching
  - fullness

WARNING

Reye's syndrome

Children and teenagers who have or are recovering from chicken pox or flu-like symptoms should not use this product. When using this product, if changes in behavior with nausea and vomiting occur, consult a doctor because these symptoms could be an early sign of Reye's Syndrome a rare but serious illness.

Allergy alert

Contains salicylate. Do not take if you are:

- allergic to salicylates (including aspirin)
- taking other salicylate products

Do not use if you have

- bloody or black stool
- an ulcer
- a bleeding problem

Ask a doctor before use if you have

- fever
- mucus in the stool

Ask a doctor or pharmacist if you are taking any drug for

- anticoagulation (thinning of the blood)
- diabetes
- gout
- arthritis

Stop use and ask a doctor if

- symptoms get worse
- ringing in the ears or loss of hearing occurs
- diarrhea lasts more than 2 days

When using this product a temporary and harmless darkening of the tongue and/or stool may occur. Stool darkening should not be confused with melena.

PREGNANCY OR BREAST FEEDING

If pregnant or breast-feeding, ask a health professional before use.

KEEP OUT OF REACH OF CHILDREN

Keep this and all drugs out of reach of children. In case of accidental overdose, contact a physician or poison control center immediately.

DIRECTIONS

- do not use more than directed
- chew or crush tablets completely before swallowing
- do not swallow tablets whole
- use until diarrhea stops but not more than 2 days
- drink plenty of clear fluids to help prevent dehydration, which may accompany diarrhea
- do not exceed 16 tablets in 24 hours

Adults and children: (12 years and older) Chew 2 tablets every 1/2 to 1 hour or 4 tablets every hour as needed.

Children under 12 years: Do not give to children under 12 years of age.

OTHER INFORMATION

- Phenylketonurics: contains phenylalanine 1.1mg per tablet
- each tablet contains 73mg of elemental calcium
- store at room temperature 59º-86ºF (15º-30ºC)
- tamper-evident sealed packets
- do not use any opened or torn packets

PRINCIPAL DISPLAY PANEL - Kit Carton

REMEDY PACK

DRUG FACTS

www.theremedypack.com